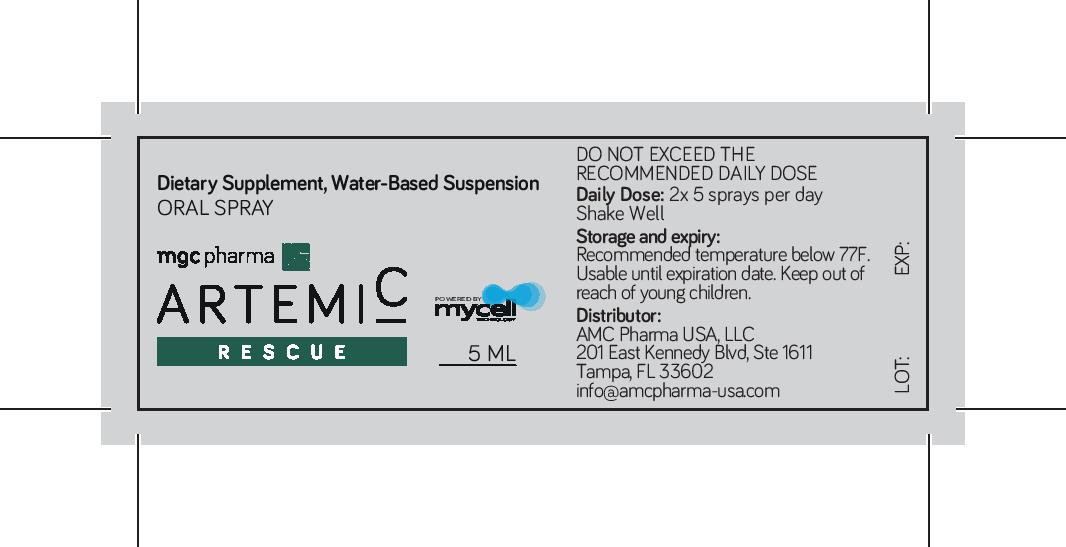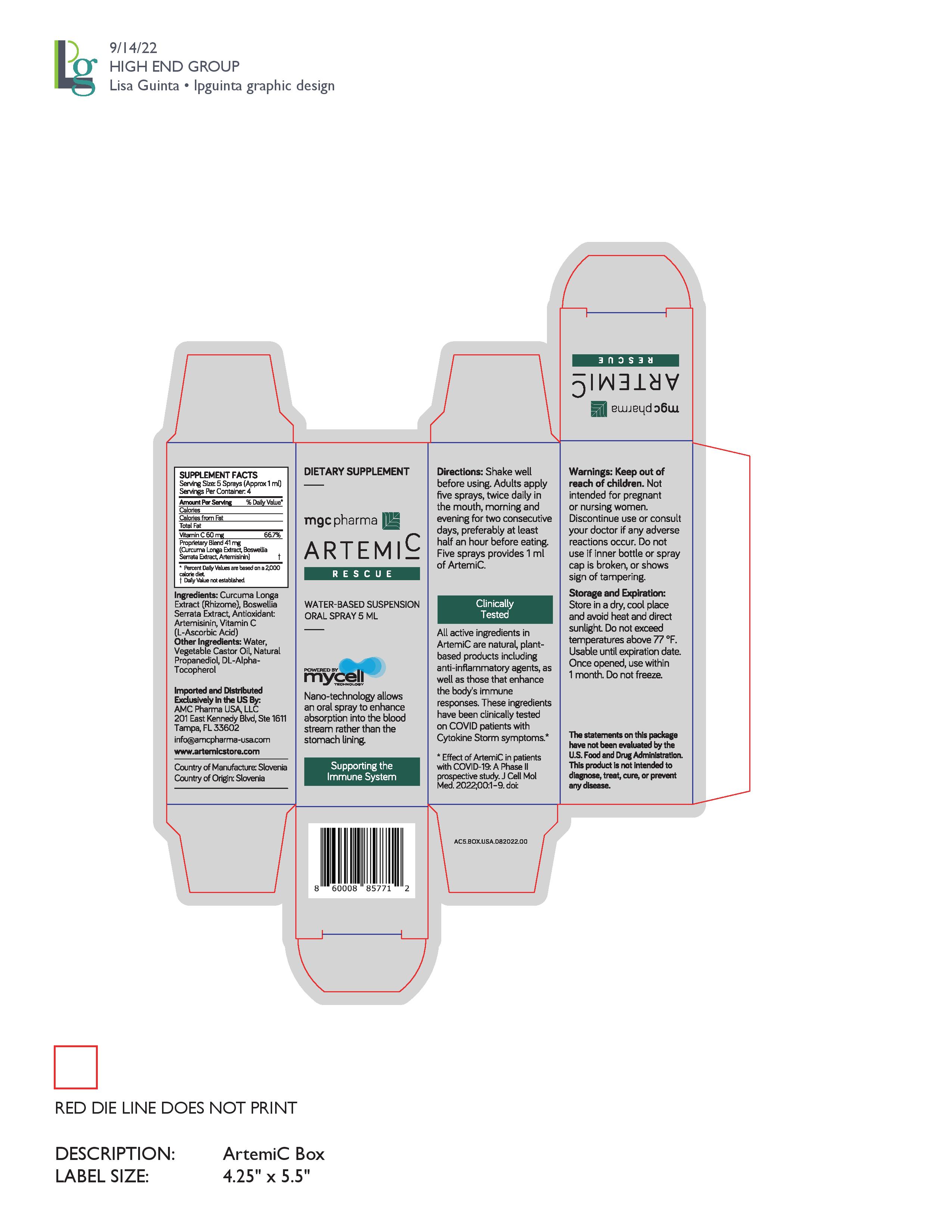 DRUG LABEL: ArtemiC Rescue
NDC: 83278-001 | Form: SPRAY, SUSPENSION
Manufacturer: AMC Pharma LLC
Category: otc | Type: HUMAN OTC DRUG LABEL
Date: 20240705

ACTIVE INGREDIENTS: ARTEMISININ 0.6 g/100 g; CURCUMIN 2 g/100 g; ASCORBIC ACID 6 g/100 g; BOSWELLIA SACRA BARK 1.5 g/100 g
INACTIVE INGREDIENTS: .ALPHA.-TOCOPHEROL, DL- 0.3 g/100 g; WATER 89 g/100 g; PROPANEDIOL 0.3 g/100 g; CASTOR OIL 0.3 g/100 g

DESCRIPTION

Water-based suspension, dietary supplement Oral Spray

ACTIVE INGREDIENT

Curcuma Longa Extract, Boswellia SerrataExtract, Antioxidant Artemisinin,Vitamin C (L-Ascorbic Acid)

INACTIVE INGREDIENT

Water, Vegetable Castor Oil, Natural Propanediol, DL-Alpha-Tocopherol

DOSAGE AND ADMINISTRATION

5 sprays provides 1 ml of ArtemiC. Servings per container: 4

INSTRUCTIONS FOR USE

Shake well before using. Adults apply 5 sprays, twice daily in the mouth, morning and evening for 2 consecutive days.preferably at least half hour before eating.

Keep out of reach of children. Not intended for pregnant or nursing woman. Discontinue use or consult your doctor if any adverse reactions occur. Do not use if inner bottle or spray cap is broken, or shows sign of tampering.

Keep Out of Reach of Children.

STORAGE AND HANDLING

Store in a dry, cool place and avoid heat and direct sunlight. Do not exceed temperatures above 77 deg F. Usable until expiration date. Once opened, use witjin 1 month. Do not freeze.

INDICATIONS AND USAGE

Adults apply 5 sprays, twice daily, into mouth.

PURPOSE

Dietary supplement to support the immune system.

PACKAGE LABEL

NDC 83278-001-05

Bottle label NDC 83278-001-05